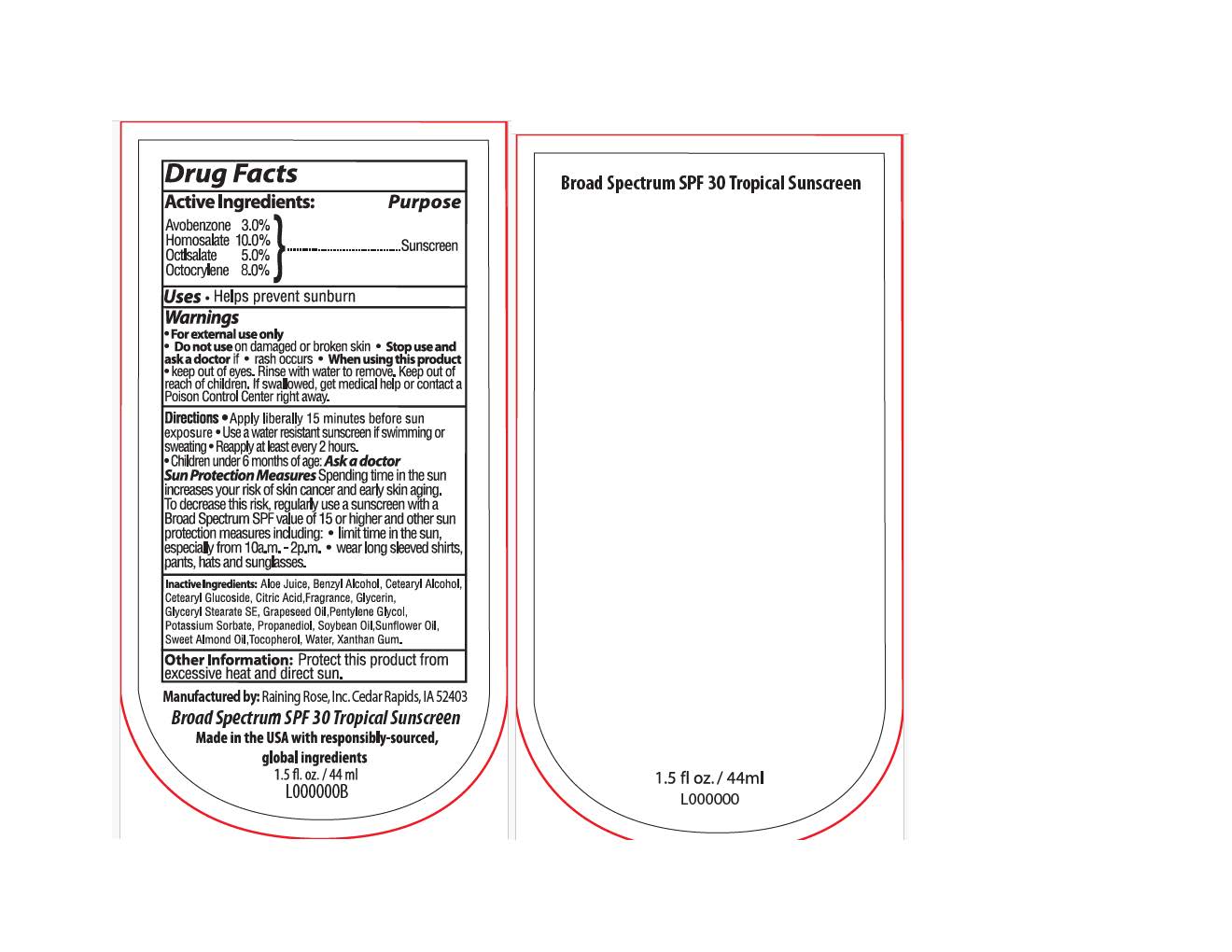 DRUG LABEL: Broad Spectrum SPF 30 Tropical Sunscreen
NDC: 65692-0590 | Form: LOTION
Manufacturer: Raining Rose, Inc
Category: otc | Type: HUMAN OTC DRUG LABEL
Date: 20250210

ACTIVE INGREDIENTS: HOMOSALATE 10 g/100 mL; OCTISALATE 5 g/100 mL; OCTOCRYLENE 8 g/100 mL; AVOBENZONE 3 g/100 mL
INACTIVE INGREDIENTS: GLYCERIN; PENTYLENE GLYCOL; XANTHAN GUM; BENZYL ALCOHOL; CITRIC ACID; VITIS VINIFERA (GRAPE) SEED OIL; PROPANEDIOL; SOYBEAN OIL; GLYCERYL STEARATE SE; ALOE BARBADENSIS LEAF JUICE; CETEARYL ALCOHOL; WATER; TOCOPHEROL; SUNFLOWER OIL; CETEARYL GLUCOSIDE; POTASSIUM SORBATE; PRUNUS AMYGDALUS DULCIS (SWEET ALMOND) OIL

ACTIVE INGREDIENT

Avobenzone 3%

Homosalate 10%

Octisalate 5%

Octocrylene 8%

PURPOSE

Sunscreen

WARNINGS

For external use only.

Do not use on damaged or broken skin.

Stop use and ask a doctor if rash occurs.

When using this product Keep out of eyes. Rinse well with water to remove.

Keep out of reach of children.

If swallowed, get medical help or contact a Poison Control Center right away.

DOSAGE AND ADMINISTRATION

Apply liberally 15 minutes before sun exposure

Use a water resistant sunscreen if swimming or sweating

Reapply at least every 2 hours
Children under 6 months of age: Ask a doctor

INACTIVE INGREDIENT

Aloe Juice, Benzyl Alcohol, Cetearyl Alcohol, Cetearyl Glucoside, Citric Acid, Fragrance, Glycerin, Glyceryl Stearate SE, Grapeseed Oil, Pentylene Gycol, Potassium Sorbate, Propanediol, Soybean Oil, Sunflower Oil, Sweet Amond Oil, Tocopherol, Water, Xanthan Gum.

INDICATIONS AND USAGE

Helps prevent sunburn